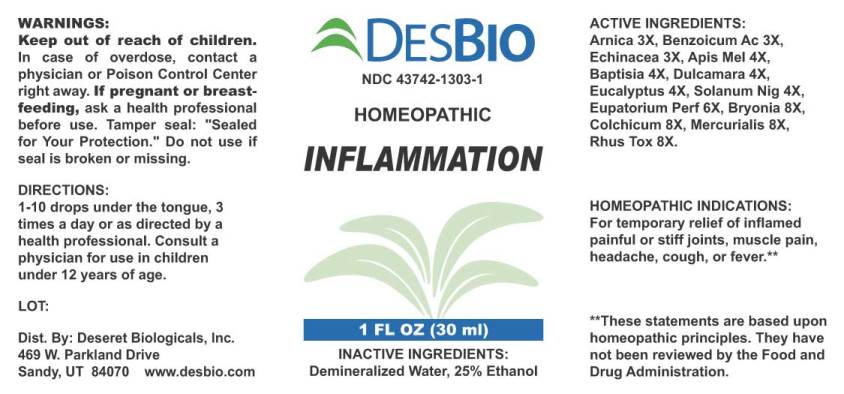 DRUG LABEL: Inflammation
NDC: 43742-1303 | Form: LIQUID
Manufacturer: Deseret Biologicals, Inc.
Category: homeopathic | Type: HUMAN OTC DRUG LABEL
Date: 20240305

ACTIVE INGREDIENTS: ARNICA MONTANA WHOLE 3 [hp_X]/1 mL; BENZOIC ACID 3 [hp_X]/1 mL; ECHINACEA ANGUSTIFOLIA WHOLE 3 [hp_X]/1 mL; APIS MELLIFERA 4 [hp_X]/1 mL; BAPTISIA TINCTORIA ROOT 4 [hp_X]/1 mL; SOLANUM DULCAMARA TOP 4 [hp_X]/1 mL; EUCALYPTUS GLOBULUS LEAF 4 [hp_X]/1 mL; SOLANUM NIGRUM WHOLE 4 [hp_X]/1 mL; EUPATORIUM PERFOLIATUM FLOWERING TOP 6 [hp_X]/1 mL; BRYONIA ALBA ROOT 8 [hp_X]/1 mL; COLCHICUM AUTUMNALE BULB 8 [hp_X]/1 mL; MERCURIALIS PERENNIS WHOLE 8 [hp_X]/1 mL; TOXICODENDRON PUBESCENS LEAF 8 [hp_X]/1 mL
INACTIVE INGREDIENTS: WATER; ALCOHOL

Drug Facts:

ACTIVE INGREDIENTS:

Arnica Montana 3X, Benzoicum Acidum 3X, Echinacea (Angustifolia) 3X, Apis Mellifica 4X, Baptisia Tinctoria 4X, Dulcamara 4X, Eucalyptus Globulus 4X, Solanum Nigrum 4X, Eupatorium Perfoliatum 6X, Bryonia (Alba) 8X, Colchicum Autumnale 8X, Mercurialis Perennis 8X, Rhus Tox 8X.

HOMEOPATHIC INDICATIONS:

For temporary relief of inflamed painful or stiff joints, muscle pain, headache, cough, or fever.**

**These statements are based upon homeopathic principles. They have not been reviewed by the Food and Drug Administration.

WARNINGS:

Keep out of reach of children. In case of overdose, contact physician or Poison Control Center right away.

If pregnant or breast-feeding, ask a health professional before use.

Tamper seal: "Sealed for Your Protection." Do not use if seal is broken or missing.

Keep out of reach of children. In case of overdose, contact physician or Poison Control Center right away.

DIRECTIONS:

1-10 drops under the tongue, 3 times a day or as directed by a health professional. Consult a physician for use in children under 12 years of age.

HOMEOPATHIC INDICATIONS:

For temporary relief of inflamed painful or stiff joints, muscle pain, headache, cough, or fever.**

**These statements are based upon homeopathic principles. They have not been reviewed by the Food and Drug Administration.

INACTIVE INGREDIENTS:

Demineralized Water, 25% Ethanol

QUESTIONS:

Dist. By: Deseret Biologicals, Inc.

469 W. Parkland Drive

Sandy, UT 84070 www.desbio.com

PACKAGE LABEL DISPLAY:

DESBIO

NDC 43742-1303-1

HOMEOPATHIC

INFLAMMATION

1 FL OZ (30 ml)